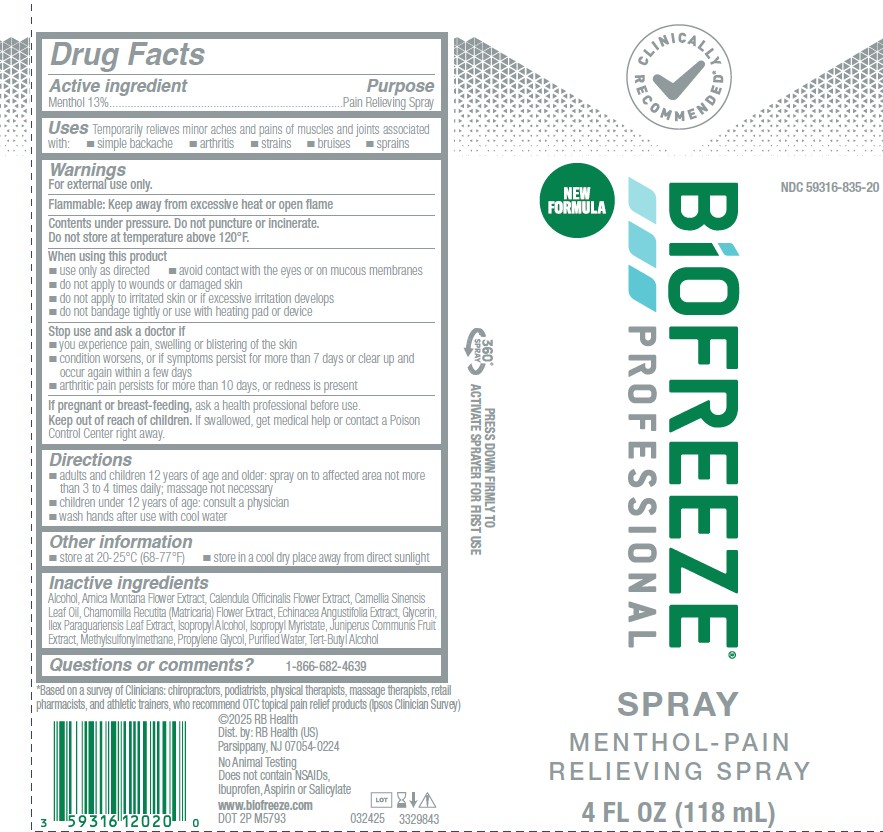 DRUG LABEL: Biofreeze
NDC: 59316-835 | Form: SPRAY
Manufacturer: RB Health (US) LLC
Category: otc | Type: HUMAN OTC DRUG LABEL
Date: 20260114

ACTIVE INGREDIENTS: MENTHOL 130 mg/1 mL
INACTIVE INGREDIENTS: PROPYLENE GLYCOL; ISOPROPYL ALCOHOL; TERT-BUTYL ALCOHOL; ARNICA MONTANA FLOWER; CALENDULA OFFICINALIS FLOWER; CHAMOMILE; DIMETHYL SULFONE; ALCOHOL; ILEX PARAGUARIENSIS LEAF; ISOPROPYL MYRISTATE; JUNIPER BERRY; WATER; ECHINACEA ANGUSTIFOLIA WHOLE; TEA LEAF OIL; GLYCERIN

Biofreeze Spray

Active Ingredients:

Menthol 13%

Purpose:

Pain Relieving Spray

Uses

Temporarily relieves minor aches and pains of muscles and joints associated
with: 􀂄 simple backache 􀂄 arthritis 􀂄 strains 􀂄 bruises 􀂄 sprains

Warnings

For external use only.

Flammable:

Keep away from excessive heat or open flame.

Contents Under Pressure. Do Not Punture Or Incinerate Do Not Store At Temperature Above 120°F

Ask a Doctor Before using If You have:

■ you experience pain, swelling or blistering of the skin
■ condition worsens, or if symptoms persist for more
than 7 days or clear up and occur again within a few
days
■ arthritic pain persists for more than 10 days, or
redness is present

When Using This Product

􀂄 use only as directed

􀂄 avoid contact with the eyes or on mucous membranes
􀂄 do not apply to wounds or damaged skin
􀂄 do not apply to irritated skin or if excessive irritation develops
􀂄 do not bandage tightly or use with heating pad or device

Stop Use And Ask A Doctor If:

Condition worsens, or if symptoms persist for more than 7 days, or clear up and recur

If pregnant or breast-feeding:

Ask a health professional before use

Keep out of reach of children:

If accidentally ingested, get medical help or contact a Poison Control Center immediately

Directions:

Adults and children 12 years of age and older:Spray on to the affected areas not more than 4 times daily; massage not necessary
Children under 12 years of age:Consult physician

Wash hands after use with cool water

OTHER SAFETY INFORMATION

􀂄 store at 20-25°C (68-77°F)

􀂄 store in a cool dry place away from direct sunlight

Inactive Ingredients

Alcohol, Arnica Montana Flower Extract, Calendula Officinalis Flower Extract, Camellia Sinensis
Leaf Oil, Chamomilla Recutita (Matricaria) Flower Extract, Echinacea Angustifolia Extract, Glycerin,
Ilex Paraguariensis Leaf Extract, Isopropyl Alcohol, Isopropyl Myristate, Juniperus Communis Fruit
Extract, Methylsulfonylmethane, Propylene Glycol, PurifiedWater, Tert-Butyl Alcohol

Questions or Comments:

1-866-682-4639